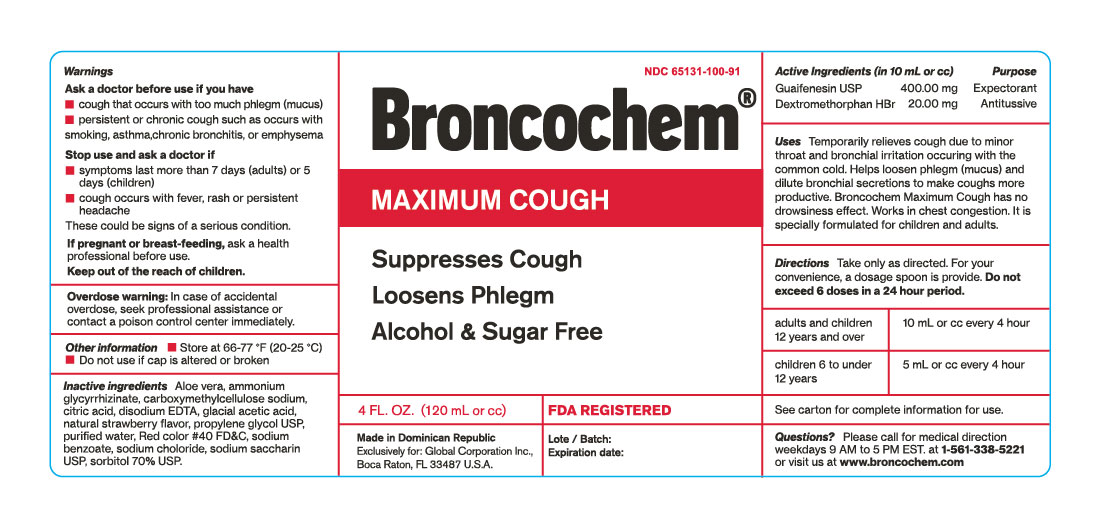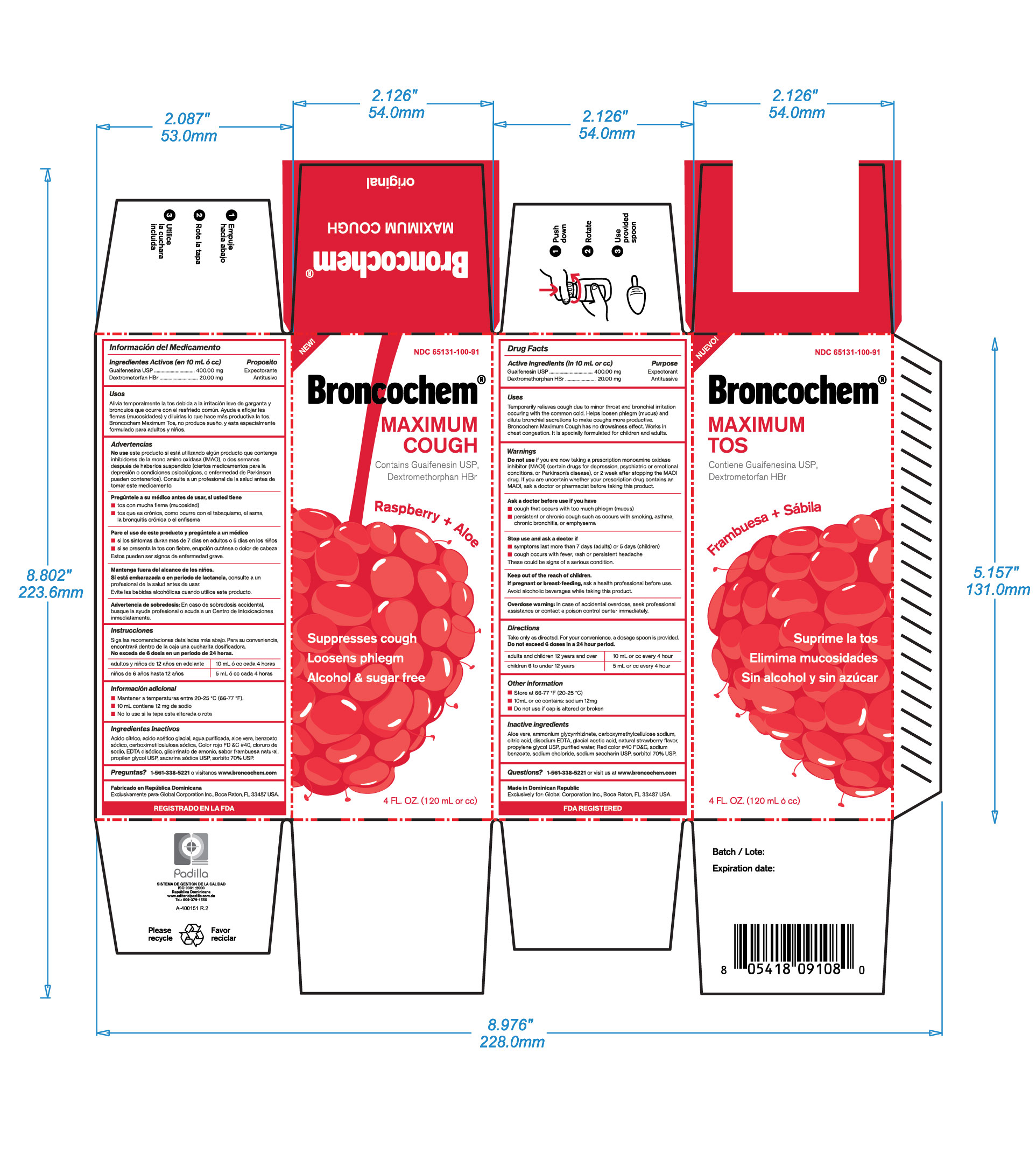 DRUG LABEL: BRONCOCHEM
NDC: 65131-100 | Form: SYRUP
Manufacturer: LABORATORIO MAGNACHEM INTERNATIONAL SRL
Category: otc | Type: HUMAN OTC DRUG LABEL
Date: 20250323

ACTIVE INGREDIENTS: DEXTROMETHORPHAN HYDROBROMIDE 20 mg/10 mL; GUAIFENESIN 400 mg/10 mL
INACTIVE INGREDIENTS: ANHYDROUS CITRIC ACID 4 mg/10 mL; SODIUM BENZOATE 20 mg/10 mL; CARBOXYMETHYLCELLULOSE SODIUM 6.8 mg/10 mL; SODIUM CHLORIDE 12 mg/10 mL; FD&C RED NO. 40 0.508 mg/10 mL; DISODIUM HEDTA 5 mg/10 mL; AMMONIUM GLYCYRRHIZATE 20 mg/10 mL; SACCHARIN SODIUM 30 mg/10 mL; ACETIC ACID 0.016 mL/10 mL; PROPYLENE GLYCOL 1.6 mL/10 mL; RASPBERRY 0.04 mL/10 mL; SORBITOL 2 mL/10 mL; ALOE VERA LEAF 20 mg/10 mL; WATER 10 mL/10 mL

BRONCOCHEM MAXIMUM COUGH

Warning Secction

Do not take this product for persitent or chronic cough such as occurs with smoking, asthma, or emphysema or if cough is accompainied with excessive phlegm (mucus) unless directed by a doctor. Persistent cough may be the sign of a serious condition. Stop use and dask a doctor if symptoms persist or last more than 5 days (children) or 7 days (adults), tends to recur, is accompained or followed by fever, headache, rash, swelling, nausea or vomiting, consult a doctor. Do not take this product if you are hypersensitive to any of the ingredients. As with any drug, if you are pregnant or nursing a baby, seek the advice of a health professional before using this product. Avoid alcoholic beverages while taking this product.

Active Ingredients

Guaifenesin

Dextromethorphan HBr

Purpose

Expectorant

Antitussive

Keep out of the reach of children

In case of accidental overdose, seek professional assistance or contact a poison control center immediately

Indications and Usage

Temporarily relieves cough due to minor throat and bronchial irritation occuring with common cold.

Helps loosen phlegm (mucus) and dilute bronchial secretions to make coughs more productive.

This new formulation with aloe results a natural cleanser, penetrates tissue, bactericidal, viruscidal, and fungicidal, enhances normal cell proliferation and moisturizes tissues (this statements are not yet evaluated by the Food and Drugs Administration "FDA")

Broncochem Maximum Cough has not drowsiness effect.

Work in chest congestion, its specially formulated for children and adults.

Dossage and Administration

Do not exceed 6 doses in a 24 hour period

Adults and children 12 years and over: (10mL or cc) every 4 hours

Children 6 years up to 12 years: (5mL or cc) every 4 hours

Drug Interactions Section

Do not use if you are now taking a prescription monoamine oxidase inhibitor (MAOI), (certain drugs for depression, psychiatric or emotional conditions or Parkinsons disease), or 2 weeks after stopping the MAOI drug. Id you are uncertain ehether your prescription drug contains an MAOI, consult a health professional before taking this product

Inactive Ingredient Section

Aloe Vera, Ammonium Glycyrrhizinate, Citric Acid, Disodium HEDTA, Glacial Acetic Acid, Strawberry flavor, Propylene Glycol, Purified Water, FD&C Red 40, Sodium Benzoate, Sodium Chloride, Sodium Saccharin, Sorbitol, Carboxymethylcellulose sodium, Total Sodium content: 12mg (in 10mL or cc)